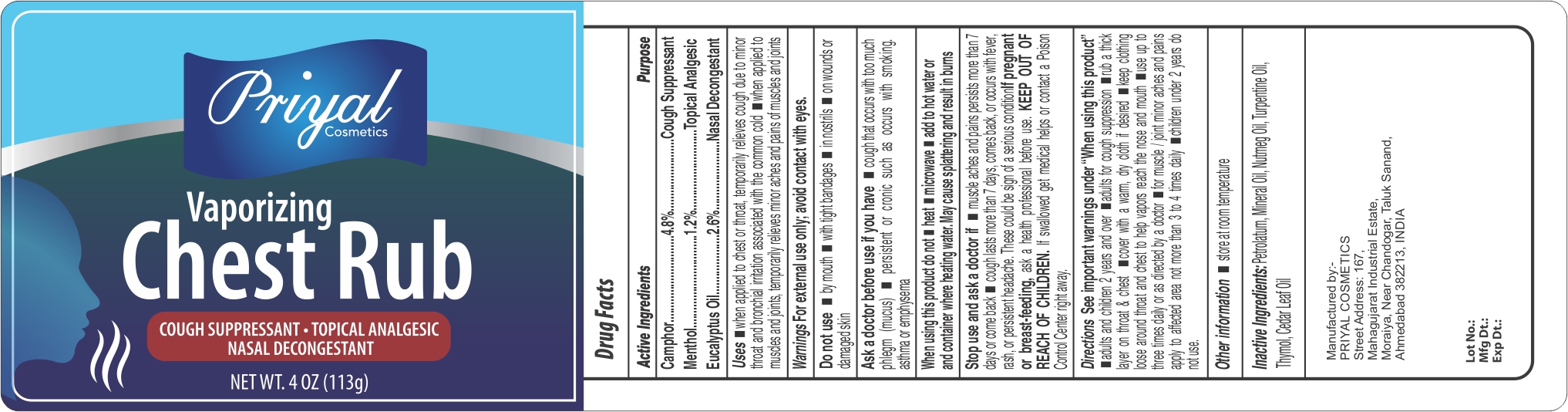 DRUG LABEL: Priyal Chestrub
NDC: 72822-015 | Form: OINTMENT
Manufacturer: Priyal Cosmetics
Category: otc | Type: HUMAN OTC DRUG LABEL
Date: 20200224

ACTIVE INGREDIENTS: CAMPHOR (NATURAL) 4.8 g/100 g; EUCALYPTUS OIL 2.6 g/100 g; MENTHOL 1.2 g/100 g
INACTIVE INGREDIENTS: MINERAL OIL; PETROLATUM; CEDAR LEAF OIL; TURPENTINE OIL; NUTMEG OIL; THYMOL

Priyal Chest Rub

ACTIVE INGREDIENT

Camphor..............4.8%

Menthol...............1.2%

Eucalyptus..........2.6%

PURPOSE

Camphor..............4.8%...............Cough Suppressant

Menthol...............1.2%................Topical Analgesic

Eucalyptus..........2.6%................Nasal Decongestant

DOSAGE AND ADMINISTRATION

See important warnings under "When using this product"

Adults and children 2 years and over:

- rub a thick layer on chest and throat
- keep clothing loose around chest/throat to help vapors reach the nose/mouth
- use up to 3 times daily or as directed by doctor

Children under 2 years of age: ask a doctor

Uses:

- On chest and throat, helps temporarily relieve cough as may occur with common cold and minor bronchial irritation
- For the temporary relief of pain associated with minor skin irritation

KEEP OUT OF REACH OF CHILDREN

Children under 2 years of age: ask a doctor

WARNINGS

For external use only. Avoid contact with eyes.

Do not take by mouth or place in nostrils

Do not use:

- by mouth
- in nostrils
- with tight bandages
- on wounds or damaged skin
- with persistent or chronic cough such as occurs with asthma, emphysema or smoking

Ask doctor if you have,

- cough that occurs with too much phiegm (mucus)

When using this product, do not

- heat
- microwave
- add to hot water or any container where heating water. May cause splattering and result in burns

Stop use and ask a doctor if:

- cough that lasts more than 7 days, comes back, or occurs with fever, rash or persistant headache. These could be signs of a serious condition

INACTIVE INGREDIENT

Petrolatum, Mineral Oil, Nutmeg Oil, Turpentine Oil, Thymol, Cedar Leaf Oil